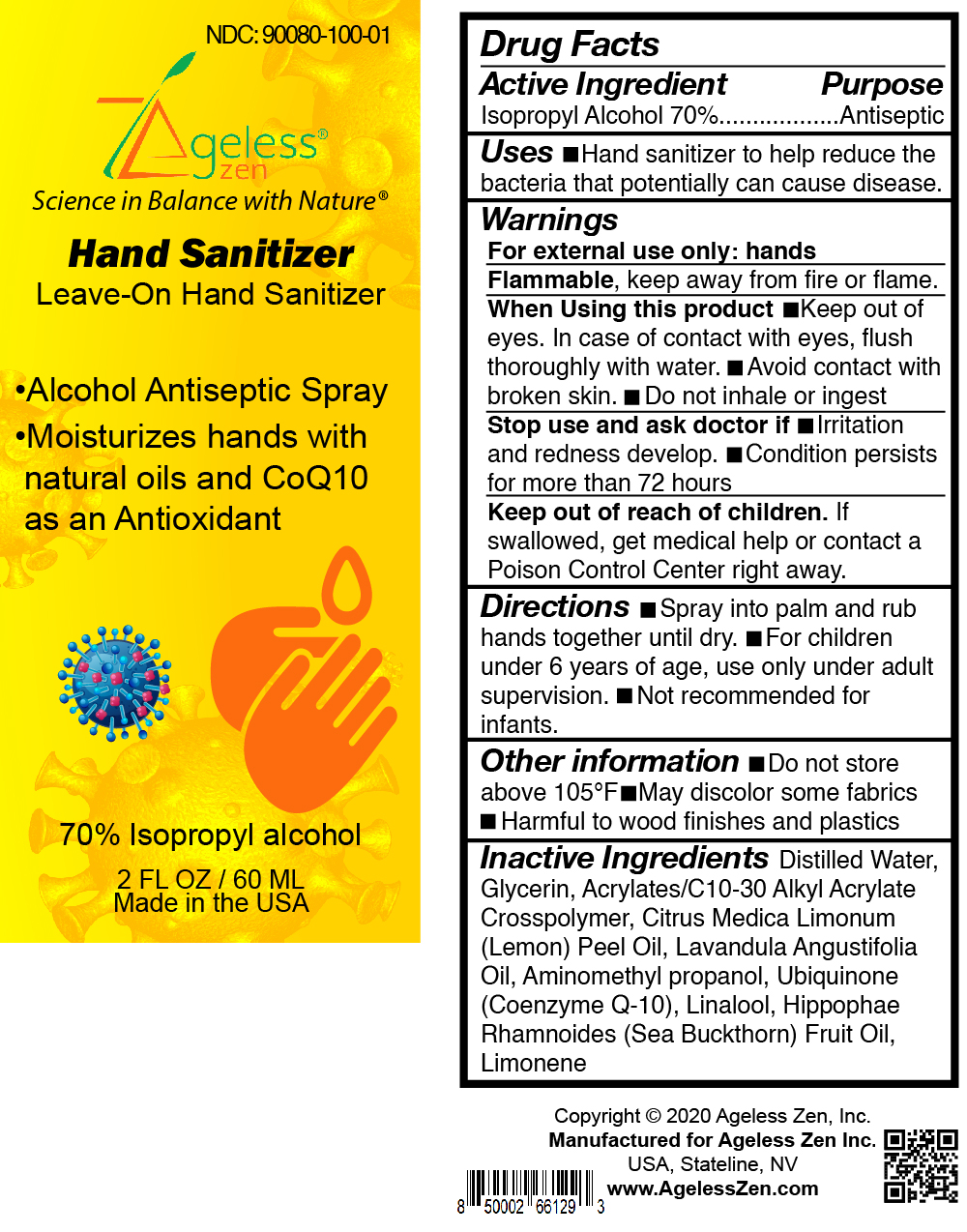 DRUG LABEL: AZ Clean and Soft Professional Leave-on Hand Sanitizer
NDC: 90080-100 | Form: SPRAY
Manufacturer: Ageless Zen Inc.
Category: otc | Type: HUMAN OTC DRUG LABEL
Date: 20201110

ACTIVE INGREDIENTS: ISOPROPYL ALCOHOL 70 mL/60 mL
INACTIVE INGREDIENTS: WATER; GLYCERIN; CARBOMER INTERPOLYMER TYPE A (ALLYL SUCROSE CROSSLINKED); CITRUS MEDICA FRUIT; LAVANDULA ANGUSTIFOLIA FLOWER; AMINOMETHYLPROPANOL; UBIDECARENONE; LINALOOL, (+/-)-; HIPPOPHAE RHAMNOIDES FRUIT; LIMONENE, (+/-)-

Ageless Zen Leave-on Hand Sanitizer

Active Ingredient

Isopropyl alcohol 70% v/v. Purpose: Antiseptic

Purpose

Antiseptic spray

Uses

Hand Sanitizer to help reduce bacteria that potentially can cause disease

Warnings

For external use only: hands.

Flammable, keep away from fire or flame.

When using this product

keep out of eyes. In case of contact with eyes, flush thoroughly with water. Avoid contact with broken skin. Do not inhale or ingest

Stop use and ask a doctor if

Irritation and redness develop Condition persists for more than 72 hours.

Directions

Spray into palm and rub hands together until dry. For children under 6 years of age, use only under adult supervision. Not recommended for infants

Other information

Do not store above 105F. May discolor some fabrics. Harmful to wood finishes and plastics.

Inactive ingredients

Distilled Water, Glycerin, Acrylates/C10-30 Alkyl Acrylate Crosspolymer, Citrus Medica Limonum (Lemon) Peel Oil, Lavandula Angustifolia Oil, Aminomethyl Propanol, Ubiquinone (Coenzyme Q-10), Linalool, Hippophae Rhamnoides (sea buckthorn) Fruit Oil, Limonene

Ageless Zen Hand Sanitizer Leave On hand sanitizer spray

Alcohol Antiseptic Spray
Moisturizes hands with natural oils and CoQ10 as an Antioxidant

70% isopropyl alcohol

2FL OZ /60 ML